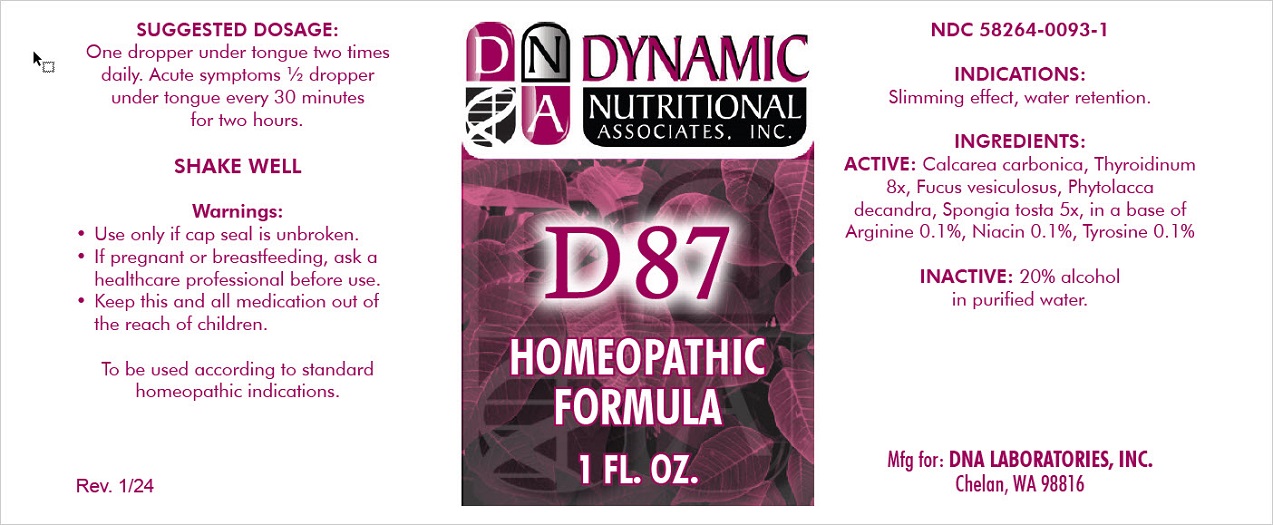 DRUG LABEL: D-87
NDC: 58264-0093 | Form: SOLUTION
Manufacturer: DNA Labs, Inc.
Category: homeopathic | Type: HUMAN OTC DRUG LABEL
Date: 20250113

ACTIVE INGREDIENTS: PHYTOLACCA AMERICANA ROOT 5 [hp_X]/1 mL; SPONGIA OFFICINALIS SKELETON, ROASTED 5 [hp_X]/1 mL; FUCUS VESICULOSUS 5 [hp_X]/1 mL; THYROID, UNSPECIFIED 8 [hp_X]/1 mL; OYSTER SHELL CALCIUM CARBONATE, CRUDE 8 [hp_X]/1 mL; ARGININE 4 [hp_X]/1 mL; TYROSINE 4 [hp_X]/1 mL; NIACIN 4 [hp_X]/1 mL
INACTIVE INGREDIENTS: ALCOHOL; WATER

D-87

NDC 58264-0093-1

INDICATIONS

PURPOSE

Slimming effect, water retention.

INGREDIENTS

ACTIVE

Phytolacca decandra 5x, Spongia tosta 5x, Fucus vesiculosus 5x, Thyroidinum 8x, Calcarea carbonica 8x, in a base of Arginine 0.1%, Tyrosine 0.1%, Niacin 0.1%

INACTIVE

20% alcohol in purified water.

SUGGESTED DOSAGE

One dropper under tongue two times daily. Acute symptoms ½ dropper under tongue every 30 minutes for two hours.

STORAGE AND HANDLING

SHAKE WELL

Warnings

- Use only if cap seal is unbroken.

PREGNANCY OR BREAST FEEDING

- If pregnant or breastfeeding, ask a healthcare professional before use.

KEEP OUT OF REACH OF CHILDREN

- Keep this and all medication out of the reach of children.

To be used according to standard homeopathic indications.

PRINCIPAL DISPLAY PANEL - 1 FL. OZ. Bottle Label

DYNAMIC
NUTRITIONAL
ASSOCIATES, INC.

D 87

HOMEOPATHIC
STRESS FORMULA

1 FL. OZ.